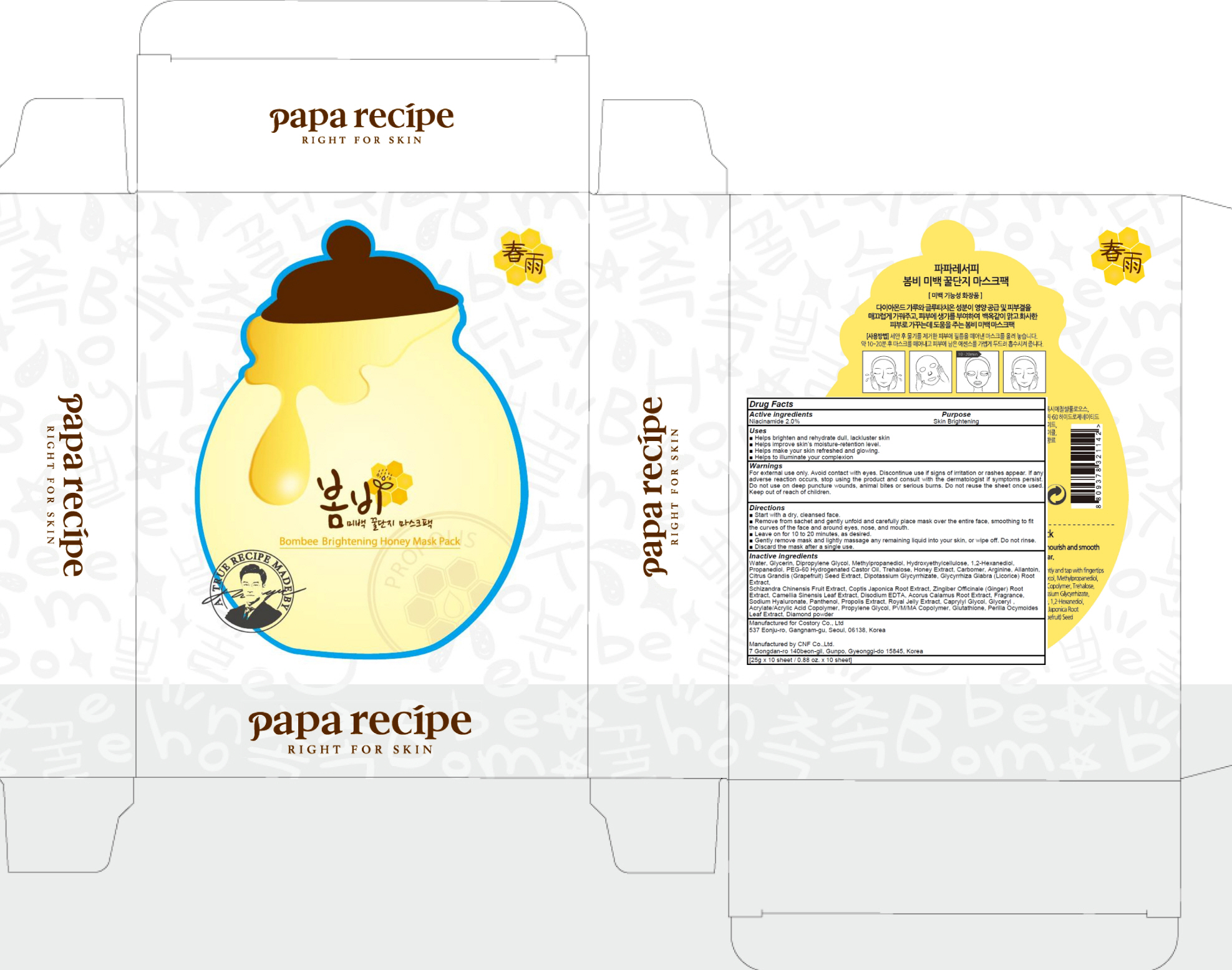 DRUG LABEL: PAPA RECIPE BOMBEE BRIGHTENING HONEY MASK PACK
NDC: 73020-040 | Form: PATCH
Manufacturer: Costory Co., Ltd
Category: otc | Type: HUMAN OTC DRUG LABEL
Date: 20190509

ACTIVE INGREDIENTS: Niacinamide 0.5 g/25 g
INACTIVE INGREDIENTS: Water; Glycerin

ACTIVE INGREDIENT

Active ingredients: Niacinamide 2.0%

INACTIVE INGREDIENT

Inactive ingredients:

Water, Glycerin, Dipropylene Glycol, Methylpropanediol, Hydroxyethylcellulose, 1,2-Hexanediol, Propanediol, PEG-60 Hydrogenated Castor Oil, Trehalose, Honey Extract, Carbomer, Arginine, Allantoin, Citrus Grandis (Grapefruit) Seed Extract, Dipotassium Glycyrrhizate, Glycyrrhiza Glabra (Licorice) Root Extract, Schizandra Chinensis Fruit Extract, Coptis Japonica Root Extract, Zingiber Officinale (Ginger) Root Extract, Camellia Sinensis Leaf Extract, Disodium EDTA, Acorus Calamus Root Extract, Fragrance, Sodium Hyaluronate, Panthenol, Propolis Extract, Royal Jelly Extract, Caprylyl Glycol, Glyceryl , Acrylate/Acrylic Acid Copolymer, Propylene Glycol, PVM/MA Copolymer, Glutathione, Perilla Ocymoides Leaf Extract, Diamond powder

PURPOSE

Purpose: Skin Brightening

WARNINGS

For external use only. Avoid contact with eyes. Discontinue use if signs of irritation or rashes appear. If any adverse reaction occurs, stop using the product and consult with the dermatologist if symptoms persist. Do not use on deep puncture wounds, animal bites or serious burns. Do not reuse the sheet once used. Keep out of reach of children.

KEEP OUT OF REACH OF CHILDREN

Uses

■ Helps brighten and rehydrate dull, lackluster skin
■ Helps improve skin’s moisture-retention level.
■ Helps make your skin refreshed and glowing.
■ Helps to illuminate your complexion

Directions

■ Start with a dry, cleansed face.
■ Remove from sachet and gently unfold and carefully place mask over the entire face, smoothing to fit the curves of the face and around eyes, nose, and mouth.
■ Leave on for 10 to 20 minutes, as desired.
■ Gently remove mask and lightly massage any remaining liquid into your skin, or wipe off. Do not rinse.
■ Discard the mask after a single use.